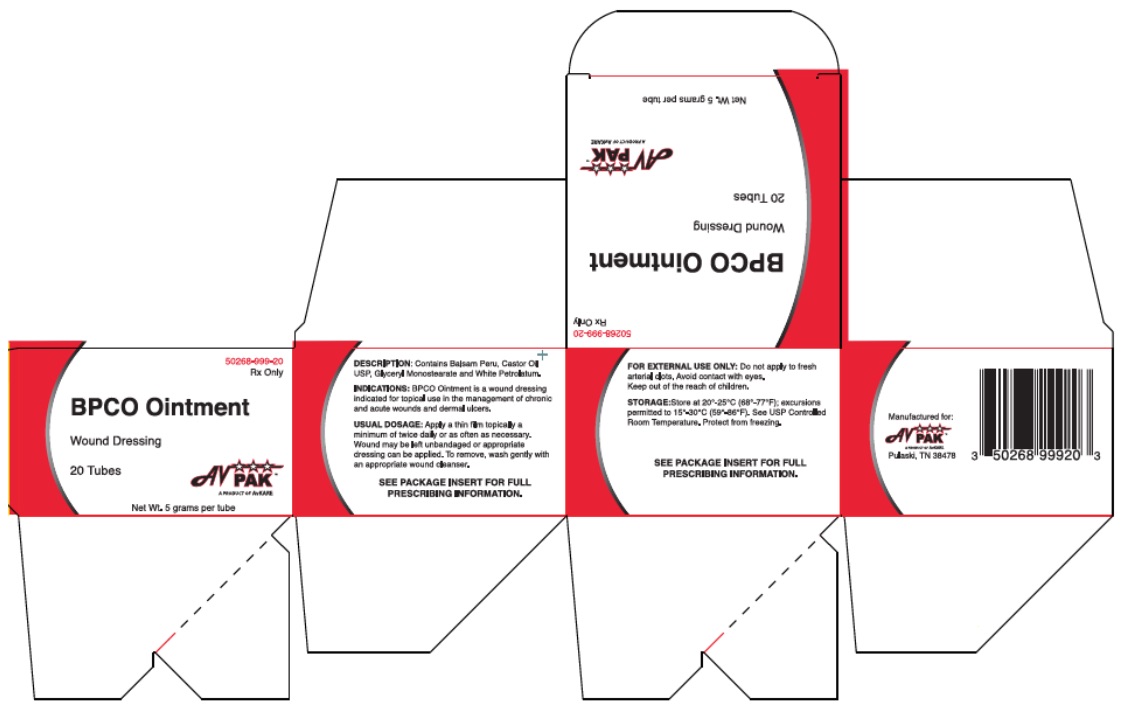 DRUG LABEL: BPCO Ointment
NDC: 50268-999
Manufacturer: AVPAK
Category: other | Type: MEDICAL DEVICE
Date: 20230901
INACTIVE INGREDIENTS: CASTOR OIL; BALSAM PERU; GLYCERYL MONOSTEARATE; PETROLATUM

BPCO Ointment

Wound Dressing
Rx Only

DESCRIPTION

DESCRIPTION: BPCO Ointment contains Balsam Peru, Castor Oil USP, Glyceryl Monostearate and White Petrolatum.

ACTION: BPCO Ointment provides a moist wound environment and acts as a protective wound covering.

INDICATIONS AND USAGE

INDICATIONS: BPCO Ointment is a wound dressing for topical use used to manage chronic and acute wounds, and dermal ulcers.

CONTRAINDICATIONS

CONTRAINDICATIONS: BPCO Ointment is contraindicated in persons who have shown hypersensitivity to Balsam Peru, Petrolatum or any of the other ingredients used in this ointment.

USES: BPCO Ointment is easy to apply. The wound may be left open or appropriate dressing applied. Please note that wounds generally heal poorly in the presence of hemoglobin or zinc deficiency.

WARNINGS

WARNING: FOR EXTERNAL USE ONLY: Do not apply to fresh arterial clots. Avoid contact with eyes. Keep tightly closed. Use only as directed by a physician. When applied to a sensitive area, a temporary stinging may occur. Keep out of the reach of children.

DOSAGE AND ADMINISTRATION

USUAL DOSAGE: Apply a thin film of BPCO Ointment topically a minimum of twice daily or as often as necessary. Wound may be left unbandaged or appropriate dressing can be applied. To remove, wash gently with an appropriate wound cleanser.

HOW SUPPLIED: BPCO Ointment is supplied as follows:

5 gram tube 20 per carton | 50268-999-20

STORAGE AND HANDLING

STORAGE: Store at 20-25ºC (68-77ºF); excursions permitted to 15-30ºC (59-86ºF). Brief exposure to temperatures up to 40°C (104°F) may be tolerated provided the mean kinetic temperature does not exceed 25°C (77°F); however such exposure should be minimized. See USP Controlled Room Temperature. Protect from freezing.

See carton and crimp for lot number and expiration date.

Manufactured for:
AvKARE, Inc.
Pulaski, TN 38478
Toll Free: 1.855.361.3993
AV 10/19

PRINCIPAL DISPLAY PANEL - 20 Tube Carton

Product Code 50268-999-20 Rx only

BPCO Ointment

Wound Dressing

20 Tubes